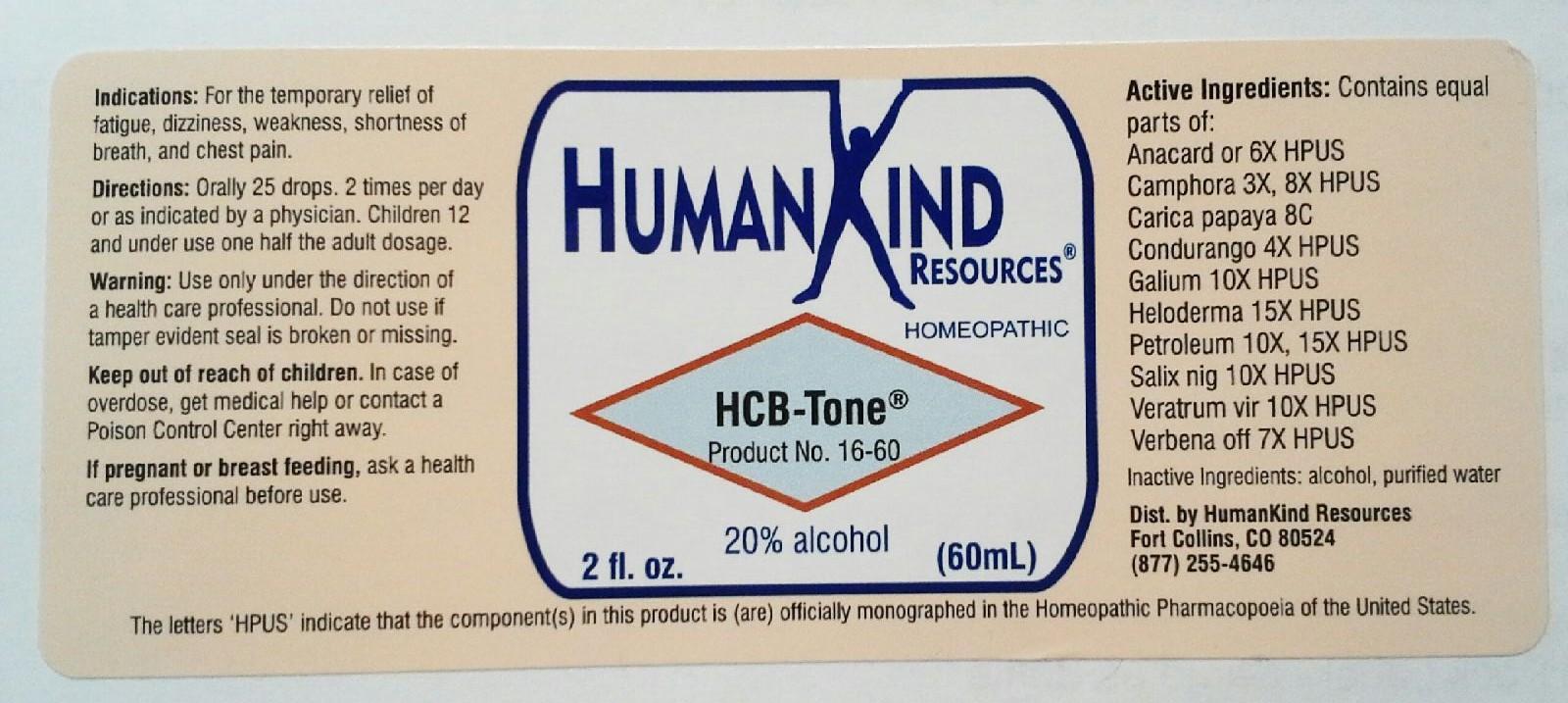 DRUG LABEL: HCB-Tone
NDC: 64616-094 | Form: LIQUID
Manufacturer: Vitality Works, Inc.
Category: homeopathic | Type: HUMAN OTC DRUG LABEL
Date: 20251217

ACTIVE INGREDIENTS: VERBENA OFFICINALIS 7 [hp_X]/1 mL; SEMECARPUS ANACARDIUM JUICE 6 [hp_X]/1 mL; CAMPHOR (NATURAL) 9 [hp_X]/1 mL; PAPAYA SEED 8 [hp_C]/1 mL; MARSDENIA CONDURANGO BARK 4 [hp_X]/1 mL; GALIUM APARINE 10 [hp_X]/1 mL; HELODERMA HORRIDUM VENOM 15 [hp_X]/1 mL; KEROSENE 15 [hp_X]/1 mL; SALIX NIGRA BARK 10 [hp_X]/1 mL; VERATRUM VIRIDE ROOT 10 [hp_X]/1 mL
INACTIVE INGREDIENTS: ALCOHOL; WATER

HCB-Tone

HCB-Tone

Anacardium Orientale 6X Heloderma 15X

Camphora 3X, 9X Petroleum 10X, 15X

Carica Papaya 8C Salix Nigra 10X

Condurango 4X Veratrum Viride 10X

Galium Aparine 10X Verbena Officinalis 7X

HCB-Tone

Alcohol, Purified Water

HCB-Tone

Use only under the direction of a health care professional. Do not use if tamper evident seal is broken or missing.

HCB-Tone

Keep out of reach of children. In case of overdose, get medical help or contact a Poison Control Certer right away.

HCB-Tone

For the temporary relief of fatigue, dizziness, weakness, shortness of breath and chest pain.

HCB-Tone

Orally 25 drops, 2 times per day or as indicated by a physician. Children 12 and under use one half the adult dosage.

HCB-Tone

Aids in heart, circulatory and blood assistance.